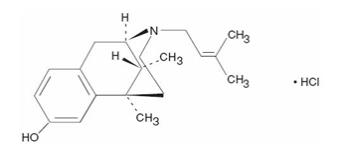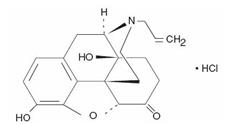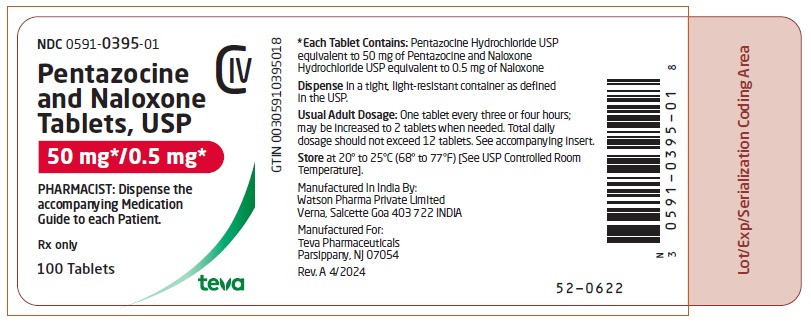 DRUG LABEL: Pentazocine and naloxone
NDC: 0591-0395 | Form: TABLET
Manufacturer: Actavis Pharma, Inc.
Category: prescription | Type: HUMAN PRESCRIPTION DRUG LABEL
Date: 20251031
DEA Schedule: CIV

ACTIVE INGREDIENTS: PENTAZOCINE HYDROCHLORIDE 50 mg/1 1; NALOXONE HYDROCHLORIDE 0.5 mg/1 1
INACTIVE INGREDIENTS: SILICON DIOXIDE; CALCIUM PHOSPHATE, DIBASIC, ANHYDROUS; D&C YELLOW NO. 10; FD&C BLUE NO. 1 ALUMINUM LAKE; FD&C YELLOW NO. 6; MAGNESIUM STEARATE; CELLULOSE, MICROCRYSTALLINE; STARCH, CORN; SODIUM LAURYL SULFATE

Pentazocine and Naloxone Tablets, USP CIV

Analgesic for Oral Use Only

BOXED WARNING

WARNING: SERIOUS AND LIFE-THREATENING RISKS FROM USE OF PENTAZOCINE AND NALOXONE TABLETS

Addiction, Abuse, and Misuse

Because the use of Pentazocine and Naloxone Tablets exposes patients and other users to the risks of opioid addiction, abuse, and misuse, which can lead to overdose and death, assess each patient’s risk prior to prescribing and reassess all patients regularly for the development of these behaviors and conditions [see WARNINGS].

Life-Threatening Respiratory Depression

Serious, life-threatening, or fatal respiratory depression may occur with use of Pentazocine and Naloxone Tablets, especially during initiation or following a dosage increase. To reduce the risk of respiratory depression, proper dosing and titration of Pentazocine and Naloxone Tablets are essential [see WARNINGS].

Accidental Ingestion

Accidental ingestion of even one dose of Pentazocine and Naloxone Tablets, especially by children, can result in a fatal overdose of Pentazocine [see WARNINGS].

Risks From Concomitant Use With Benzodiazepines Or Other CNS Depressants

Concomitant use of opioids with benzodiazepines or other central nervous system (CNS) depressants, including alcohol, may result in profound sedation, respiratory depression, coma, and death. Reserve concomitant prescribing of Pentazocine and Naloxone Tablets and benzodiazepines or other CNS depressants for use in patients for whom alternative treatment options are inadequate [see WARNINGS, PRECAUTIONS; Drug Interactions].

Neonatal Opioid Withdrawal Syndrome (NOWS)

Advise pregnant women using opioids for an extended period of time of the risk of Neonatal Opioid Withdrawal Syndrome, which may be life-threatening if not recognized and treated. Ensure that management by neonatology experts will be available at delivery [see WARNINGS].

Opioid Analgesic Risk Evaluation and Mitigation Strategy (REMS)

Healthcare providers are strongly encouraged to complete a REMS-compliant education program and to counsel patients and caregivers on serious risks, safe use, and the importance of reading the Medication Guide with each prescription [see Warnings].

DESCRIPTION

Pentazocine and Naloxone Tablets, USP contain pentazocine hydrochloride, USP, a partial opioid agonist, equivalent to 50 mg base and is a member of the benzazocine series (also known as the benzomorphan series), and naloxone hydrochloride, USP, an opioid antagonist equivalent to 0.5 mg base.

Pentazocine and Naloxone Tablets, USP are an analgesic for oral administration.

Chemically, pentazocine hydrochloride, USP is (2R*,6R*,11R*)-1,2,3,4,5,6-Hexahydro-6,11-dimethyl-3-(3-methyl-2-butenyl)-2,6-methano-3-benzazocin-8-ol hydrochloride, a white, crystalline substance soluble in acidic aqueous solutions, and has the following structural formula:

C19H27NO·HCl Molecular Weight: 321.88

Chemically, naloxone hydrochloride, USP is Morphinan-6-one,4,5-epoxy-3,14-dihydroxy-17-(2-propenyl)-, hydrochloride, (5α)-. It is a slightly off-white powder, and is soluble in water and dilute acids, and has the following structural formula:

C19H21NO4·HCl Molecular Weight: 363.84

Inactive Ingredients: colloidal silicon dioxide, dibasic calcium phosphate, D&C Yellow No. 10 Al-lake, FD&C Blue No. 1 Al-lake, FD&C Yellow No. 6 Al-lake, magnesium stearate, microcrystalline cellulose, pregelatinized starch, and sodium lauryl sulfate.

CLINICAL PHARMACOLOGY

Mechanism of Action

Pentazocine is a mixed agonist-antagonist at opioid receptors. Pentazocine is a partial agonist at the mu opioid receptor and an agonist at the kappa opioid receptor.

Naloxone is an opioid antagonist.

Pharmacodynamics

Effects on the Central Nervous System

Pentazocine produces respiratory depression by direct action on brain stem respiratory centers. The respiratory depression involves a reduction in the responsiveness of the brain stem respiratory centers to both increases in carbon dioxide tension and electrical stimulation.

Pentazocine causes miosis, even in total darkness. Pinpoint pupils are a sign of opioid overdose but are not pathognomonic (e.g., pontine lesions of hemorrhagic or ischemic origins may produce similar findings). Marked mydriasis rather than miosis may be seen due to hypoxia in overdose situations.

Effects on the Gastrointestinal Tract and Other Smooth Muscle

Pentazocine causes a reduction in motility associated with an increase in smooth muscle tone in the antrum of the stomach and duodenum. Digestion of food in the small intestine is delayed and propulsive contractions are decreased. Propulsive peristaltic waves in the colon are decreased, while tone may be increased to the point of spasm, resulting in constipation. Other opioid-induced effects may include a reduction in biliary and pancreatic secretions, spasm of sphincter of Oddi, transient elevations in serum amylase, and opioid-induced esophageal dysfunction (OIED).

Effects on the Cardiovascular System

Pentazocine produces peripheral vasodilation which may result in orthostatic hypotension or syncope. Manifestations of histamine release and/or peripheral vasodilation may include pruritus, flushing, red eyes, sweating, and/or orthostatic hypotension.

Effects on the Endocrine System

Opioids inhibit the secretion of adrenocorticotropic hormone (ACTH), cortisol, and luteinizing hormone (LH) in humans [see ADVERSE REACTIONS]. They also stimulate prolactin, growth hormone (GH) secretion, and pancreatic secretion of insulin and glucagon.

Use of opioids for an extended period of time may influence the hypothalamic-pituitary-gonadal axis, leading to androgen deficiency that may manifest as low libido, impotence, erectile dysfunction, amenorrhea, or infertility. The causal role of opioids in the clinical syndrome of hypogonadism is unknown because the various medical, physical, lifestyle, and psychological stressors that may influence gonadal hormone levels have not been adequately controlled for in studies conducted to date [see ADVERSE REACTIONS].

Effects on the Immune System

Opioids have been shown to have a variety of effects on components of the immune system. The clinical significance of these findings is unknown. Overall, the effects of opioids appear to be modestly immunosuppressive.

Concentration–Efficacy Relationships

The minimum effective analgesic concentration will vary widely among patients, especially among patients who have been previously treated with opioid agonists. The minimum effective analgesic concentration of pentazocine for any individual patient may increase over time due to an increase in pain, the development of a new pain syndrome, and/or the development of analgesic tolerance [see DOSAGE AND ADMINISTRATION].

Concentration–Adverse Reaction Relationships

There is a relationship between increasing pentazocine plasma concentration and increasing frequency of dose-related opioid adverse reactions such as nausea, vomiting, CNS effects, and respiratory depression. In opioid-tolerant patients, the situation may be altered by the development of tolerance to opioid-related adverse reactions [see DOSAGE AND ADMINISTRATION].

Opioid Antagonist Effects

Pentazocine weakly antagonizes the analgesic effects of morphine, meperidine, and phenazocine; in addition, it produces incomplete reversal of cardiovascular, respiratory, and behavioral depression induced by morphine and meperidine. Pentazocine has about 1/50 the antagonistic activity of nalorphine. It also has sedative activity.

Naloxone when administered orally at 0.5 mg has no pharmacologic activity. Naloxone hydrochloride administered parenterally at the same dose is an antagonist to pentazocine and a pure antagonist to narcotic analgesics.

Pentazocine and Naloxone Tablets are a potent analgesic when administered orally. However, the presence of naloxone in Pentazocine and Naloxone Tablets is intended to prevent the effect of pentazocine if the product is misused by injection.

Studies in animals indicate that the presence of naloxone does not affect pentazocine analgesia when the combination is given orally. If the combination is given by injection the action of pentazocine is neutralized.

Pharmacokinetics

Onset of significant analgesia usually occurs between 15 and 30 minutes after oral administration, and duration of action is usually three hours or longer.

Pentazocine is well absorbed from the gastrointestinal tract. Concentrations in plasma coincide closely with the onset, duration, and intensity of analgesia. The time to mean peak concentration in 24 normal volunteers was 1.7 hours (range 0.5 to 4 hours) after oral administration and the mean plasma elimination half-life was 3.6 hours (range 1.5 to 10 hours).

Pentazocine is metabolized in the liver and excreted primarily in the urine. The products of the oxidation of the terminal methyl groups and glucuronide conjugates are excreted by the kidney. Elimination of approximately 60% of the total dose occurs within 24 hours. Pentazocine passes into the fetal circulation.

INDICATIONS AND USAGE

Pentazocine and Naloxone Tablets are indicated for the management of pain severe enough to require an opioid analgesic and for which alternative treatments are inadequate.

Limitations of Use

Because of the risks of addiction, abuse, misuse, overdose, and death, which can occur at any dosage or duration and persist over the course of therapy [see WARNINGS], reserve opioid analgesics, including Pentazocine and Naloxone Tablets, for use in patients for whom alternative treatment options are ineffective, not tolerated, or would be otherwise inadequate to provide sufficient management of pain.

CONTRAINDICATIONS

Pentazocine and Naloxone Tablets are contraindicated in patients with:

- Significant respiratory depression [see WARNINGS]
- Acute or severe bronchial asthma in an unmonitored setting or in the absence of resuscitative equipment [see WARNINGS]
- Patients with known or suspected gastrointestinal obstruction, including paralytic ileus [see WARNINGS]
- Patients with hypersensitivity to either pentazocine, naloxone, or any of the formulation excipients (e.g., anaphylaxis) [see WARNINGS].

WARNINGS

Addiction, Abuse, and Misuse

Pentazocine and Naloxone Tablets contain pentazocine, a Schedule IV controlled substance. As an opioid, Pentazocine and Naloxone Tablets expose users to the risks of addiction, abuse, and misuse [see DRUG ABUSE AND DEPENDENCE].

Although the risk of addiction in any individual is unknown, it can occur in patients appropriately prescribed Pentazocine and Naloxone Tablets. Addiction can occur at recommended dosages and if the drug is misused or abused. The risk of opioid-related overdose or overdose-related death is increased with higher opioid doses, and this risk persists over the course of therapy. In postmarketing studies, addiction, abuse, misuse, and fatal and non-fatal opioid overdose were observed in patients with long-term opioid use [ADVERSE REACTIONS].

Assess each patient’s risk for opioid addiction, abuse, or misuse prior to prescribing Pentazocine and Naloxone Tablets, and reassess all patients receiving Pentazocine and Naloxone Tablets for the development of these behaviors and conditions. Risks are increased in patients with a personal or family history of substance abuse (including drug or alcohol abuse or addiction) or mental illness (e.g., major depression). The potential for these risks should not, however, prevent the proper management of pain in any given patient. Patients at increased risk may be prescribed opioids such as Pentazocine and Naloxone Tablets, but use in such patients necessitates intensive counseling about the risks and proper use of Pentazocine and Naloxone Tablets along with frequent reevaluation for signs of addiction, abuse, and misuse. Consider recommending or prescribing an opioid overdose reversal agent [see WARNINGS; Life-Threatening Respiratory Depression, DOSAGE AND ADMINISTRATION; Patient Access to an Opioid Overdose Reversal Agent for the Emergency Treatment of Opioid Overdose].

Opioids are sought for nonmedical use and are subject to diversion from legitimate prescribed use. Consider these risks when prescribing or dispensing Pentazocine and Naloxone Tablets. Strategies to reduce these risks include prescribing the drug in the smallest appropriate quantity and advising the patient on careful storage of the drug during the course of treatment and proper disposal of unused drug [see PRECAUTIONS; Information for Patients]. Contact local state professional licensing board or state-controlled substances authority for information on how to prevent and detect abuse or diversion of this product.

Life-Threatening Respiratory Depression

Serious, life-threatening, or fatal respiratory depression has been reported with the use of opioids, even when used as recommended. Respiratory depression, if not immediately recognized and treated, may lead to respiratory arrest and death. Management of respiratory depression may include close observation, supportive measures, and use of opioid overdose reversal agents, depending on the patient’s clinical status [see OVERDOSAGE]. Carbon dioxide (CO2) retention from opioid-induced respiratory depression can exacerbate the sedating effects of opioids.

While serious, life-threatening, or fatal respiratory depression can occur at any time during the use of Pentazocine and Naloxone Tablets, the risk is greatest during the initiation of therapy or following a dosage increase.

To reduce the risk of respiratory depression, proper dosing and titration of Pentazocine and Naloxone Tablets are essential [see DOSAGE AND ADMINISTRATION]. Overestimating the Pentazocine and Naloxone Tablets dosage when converting patients from another opioid product can result in a fatal overdose with the first dose.

Accidental ingestion of Pentazocine and Naloxone Tablets, especially by children, can result in respiratory depression and death due to an overdose of pentazocine.

Educate patients and caregivers on how to recognize respiratory depression and emphasize the importance of calling 911 or getting emergency medical help right away in the event of a known or suspected overdose [see PRECAUTIONS; Information for Patients].

Opioids can cause sleep-related breathing disorders including central sleep apnea (CSA) and sleep-related hypoxemia. Opioid use increases the risk of CSA in a dose-dependent fashion. In patients who present with CSA, consider decreasing the opioid dosage using best practices for opioid taper [see DOSAGE AND ADMINISTRATION].

Patient Access to an Opioid Overdose Reversal Agent for the Emergency Treatment of Opioid Overdose

Inform patients and caregivers about opioid overdose reversal agents (e.g., naloxone, nalmefene). Discuss the importance of having access to an opioid overdose reversal agent, especially if the patient has risk factors for overdose (e.g., concomitant use of CNS depressants, a history of opioid use disorder, or prior opioid overdose) or if there are household members (including children) or other close contacts at risk for accidental ingestion or opioid overdose. The presence of risk factors for overdose should not prevent the management of pain in any patient [see WARNINGS].

Discuss the options for obtaining an opioid overdose reversal agent (e.g., prescription, over-the-counter, or as part of a community-based program).

There are important differences among the opioid overdose reversal agents, such as route of administration, product strength, approved patient age range, and pharmacokinetics. Be familiar with these differences, as outlined in the approved labeling for those products, prior to recommending or prescribing such an agent.

Educate patients and caregivers on how to recognize respiratory depression, and how to use an opioid overdose reversal agent for the emergency treatment of opioid overdose. Emphasize the importance of calling 911 or getting emergency medical help, even if an opioid overdose reversal agent is administered [see WARNINGS, OVERDOSAGE].

Risks from Concomitant Use with Benzodiazepines or Other CNS Depressants

Profound sedation, respiratory depression, coma, and death may result from the concomitant use of Pentazocine and Naloxone Tablets with benzodiazepines and/or other CNS depressants, including alcohol (e.g., non-benzodiazepine sedatives/hypnotics, anxiolytics, tranquilizers, muscle relaxants, general anesthetics, antipsychotics, gabapentinoids [gabapentin or pregabalin], and other opioids). Because of these risks, reserve concomitant prescribing of these drugs for use in patients for whom alternative treatment options are inadequate.

Observational studies have demonstrated that concomitant use of opioid analgesics and benzodiazepines increases the risk of drug-related mortality compared to use of opioid analgesics alone. Because of similar pharmacological properties, it is reasonable to expect similar risk with the concomitant use of other CNS depressant drugs with opioid analgesics [see PRECAUTIONS; Drug Interactions].

If the decision is made to prescribe a benzodiazepine or other CNS depressant concomitantly with an opioid analgesic, prescribe the lowest effective dosages and minimum durations of concomitant use. In patients already receiving an opioid analgesic, prescribe a lower initial dose of the benzodiazepine or other CNS depressant than indicated in the absence of an opioid, and titrate based on clinical response. If an opioid analgesic is initiated in a patient already taking a benzodiazepine or other CNS depressant, prescribe a lower initial dose of the opioid analgesic, and titrate based on clinical response. Inform patients and caregivers of this potential interaction, educate them on the signs and symptoms of respiratory depression (including sedation).

If concomitant use is warranted, consider recommending or prescribing an opioid overdose reversal agent [see WARNINGS; Life-Threatening Respiratory Depression, DOSAGE AND ADMINISTRATION; Patient Access to an Opioid Overdose Reversal Agent for the Emergency Treatment of Opioid Overdose].

Advise both patients and caregivers about the risks of respiratory depression and sedation when Pentazocine and Naloxone Tablets are used with benzodiazepines or other CNS depressants (including alcohol and illicit drugs). Advise patients not to drive or operate heavy machinery until the effects of concomitant use of the benzodiazepine or other CNS depressant have been determined. Screen patients for risk of substance use disorders, including opioid abuse and misuse, and warn them of the risk for overdose and death associated with the use of additional CNS depressants including alcohol and illicit drugs [see PRECAUTIONS; Information for Patients, Drug Interactions].

Neonatal Opioid Withdrawal Syndrome

Use of Pentazocine and Naloxone Tablets for an extended period of time during pregnancy can result in withdrawal in the neonate. Neonatal opioid withdrawal syndrome, unlike opioid withdrawal syndrome in adults, may be life-threatening if not recognized and treated, and requires management according to protocols developed by neonatology experts. Observe newborns for signs of neonatal opioid withdrawal syndrome and manage accordingly. Advise pregnant women using opioids for an extended period of time of the risk of neonatal opioid withdrawal syndrome and ensure that appropriate treatment will be available [see PRECAUTIONS; Information for Patients, Pregnancy].

Opioid Analgesic Risk Evaluation and Mitigation Strategy (REMS)

To ensure that the benefits of opioid analgesics outweigh the risks of addiction, abuse, and misuse, the Food and Drug Administration (FDA) has required a Risk Evaluation and Mitigation Strategy (REMS) for these products. Under the requirements of the REMS, drug companies with approved opioid analgesic products must make REMS-compliant education programs available to healthcare providers. Healthcare providers are strongly encouraged to do all of the following:

- Complete a REMS-compliant education program offered by an accredited provider of continuing education (CE) or another education program that includes all the elements of the FDA Education Blueprint for Health Care Providers Involved in the Management or Support of Patients with Pain.
- Discuss the safe use, serious risks, and proper storage and disposal of opioid analgesics with patients and/or their caregivers every time these medicines are prescribed. The Patient Counseling Guide (PCG) can be obtained at this link: www.fda.gov/OpioidAnalgesicREMSPCG.
- Emphasize to patients and their caregivers the importance of reading the Medication Guide that they will receive from their pharmacist every time an opioid analgesic is dispensed to them.
- Consider using other tools to improve patient, household, and community safety, such as patient-prescriber agreements that reinforce patient-prescriber responsibilities.

To obtain further information on the opioid analgesic REMS and for a list of accredited REMS CME/CE, call 800-503-0784, or log on to www.opioidanalgesicrems.com. The FDA Blueprint can be found at www.fda.gov/OpioidAnalgesicREMSBlueprint.

Opioid-Induced Hyperalgesia and Allodynia

Opioid-Induced Hyperalgesia (OIH) occurs when an opioid analgesic paradoxically causes an increase in pain, or an increase in sensitivity to pain. This condition differs from tolerance, which is the need for increasing doses of opioids to maintain a defined effect [see Dependence]. Symptoms of OIH include (but may not be limited to) increased levels of pain upon opioid dosage increase, decreased levels of pain upon opioid dosage decrease, or pain from ordinarily non-painful stimuli (allodynia). These symptoms may suggest OIH only if there is no evidence of underlying disease progression, opioid tolerance, opioid withdrawal, or addictive behavior.

Cases of OIH have been reported, both with short-term and longer-term use of opioid analgesics. Though the mechanism of OIH is not fully understood, multiple biochemical pathways have been implicated. Medical literature suggests a strong biologic plausibility between opioid analgesics and OIH and allodynia. If a patient is suspected to be experiencing OIH, carefully consider appropriately decreasing the dose of the current opioid analgesic, or opioid rotation (safely switching the patient to a different opioid moiety) [see Dosage and Administration, Warning].

Life-Threatening Respiratory Depression in Patients with Chronic Pulmonary Disease or in Elderly, Cachectic, or Debilitated Patients

The use of Pentazocine and Naloxone Tablets in patients with acute or severe bronchial asthma in an unmonitored setting or in the absence of resuscitative equipment is contraindicated.

Patients with Chronic Pulmonary Disease: Pentazocine and naloxone-treated patients with significant chronic obstructive pulmonary disease or cor pulmonale, and those with a substantially decreased respiratory reserve, hypoxia, hypercapnia, or pre-existing respiratory depression are at increased risk of decreased respiratory drive including apnea, even at recommended dosages of Pentazocine and Naloxone Tablets [see WARNINGS].

Elderly, Cachectic, or Debilitated Patients: Life-threatening respiratory depression is more likely to occur in elderly, cachectic, or debilitated patients because they may have altered pharmacokinetics or altered clearance compared to younger, healthier patients [see WARNINGS].

Regularly evaluate patients, particularly when initiating and titrating Pentazocine and Naloxone Tablets and when Pentazocine and Naloxone Tablets are given concomitantly with other drugs that depress respiration [see WARNINGS]. Alternatively, consider the use of non-opioid analgesics in these patients.

Adrenal Insufficiency

Cases of adrenal insufficiency have been reported with opioid use, more often following greater than 1 month of use. Presentation of adrenal insufficiency may include non-specific symptoms and signs including nausea, vomiting, anorexia, fatigue, weakness, dizziness, and low blood pressure. If adrenal insufficiency is suspected, confirm the diagnosis with diagnostic testing as soon as possible. If adrenal insufficiency is diagnosed, treat with physiologic replacement doses of corticosteroids. Wean the patient off of the opioid to allow adrenal function to recover and continue corticosteroid treatment until adrenal function recovers. Other opioids may be tried as some cases reported use of a different opioid without recurrence of adrenal insufficiency. The information available does not identify any particular opioids as being more likely to be associated with adrenal insufficiency.

Severe Hypotension

Pentazocine and Naloxone Tablets may cause severe hypotension including orthostatic hypotension and syncope in ambulatory patients. There is increased risk in patients whose ability to maintain blood pressure has already been compromised by a reduced blood volume or concurrent administration of certain CNS depressant drugs (e.g., phenothiazines or general anesthetics) [see PRECAUTIONS; Information for Patients]. Regularly evaluate these patients for signs of hypotension after initiating or titrating the dosage of Pentazocine and Naloxone Tablets. In patients with circulatory shock, Pentazocine and Naloxone Tablets may cause vasodilation that can further reduce cardiac output and blood pressure. Avoid the use of Pentazocine and Naloxone Tablets in patients with circulatory shock.

Risks of Use in Patients with Increased Intracranial Pressure, Brain Tumors, Head Injury, or Impaired Consciousness

In patients who may be susceptible to the intracranial effects of CO2 retention (e.g., those with evidence of increased intracranial pressure or brain tumors), Pentazocine and Naloxone Tablets may reduce respiratory drive, and the resultant CO2 retention can further increase intracranial pressure. Monitor such patients for signs of sedation and respiratory depression, particularly when initiating therapy with Pentazocine and Naloxone Tablets.

Opioids may also obscure the clinical course in a patient with a head injury. Avoid the use of Pentazocine and Naloxone Tablets in patients with impaired consciousness or coma.

Risks of Gastrointestinal Complications

Pentazocine and Naloxone Tablets are contraindicated in patients with known or suspected gastrointestinal obstruction, including paralytic ileus.

The administration of Pentazocine and Naloxone Tablets or other opioids may obscure the diagnosis or clinical course in patients with acute abdominal conditions.

Pentazocine and Naloxone Tablets may cause spasm of the sphincter of Oddi. Opioids may cause increases in serum amylase. Regularly evaluate patients with biliary tract disease, including acute pancreatitis, for worsening symptoms.

Cases of opioid-induced esophageal dysfunction (OIED) have been reported in patients taking opioids. The risk of OIED may increase as the dose and/or duration of opioids increases. Regularly evaluate patients for signs and symptoms of OIED (e.g., dysphagia, regurgitation, non-cardiac chest pain) and, if necessary, adjust opioid therapy as clinically appropriate [see CLINICAL PHARMACOLOGY].

Increased Risk of Seizures in Patients with Seizure Disorders

The pentazocine in Pentazocine and Naloxone Tablets may increase the frequency of seizures in patients with seizure disorders, and may increase the risk of seizures occurring in other clinical settings associated with seizures. Regularly evaluate patients with a history of seizure disorders for worsened seizure control during Pentazocine and Naloxone Tablets therapy.

Withdrawal

Do not rapidly reduce or abruptly discontinue Pentazocine and Naloxone Tablets in a patient physically dependent on opioids. When discontinuing Pentazocine and Naloxone Tablets in a physically dependent patient, gradually taper the dosage. Rapid tapering of Pentazocine and Naloxone Tablets in a patient physically dependent on opioids may lead to a withdrawal syndrome and return of pain [see DOSAGE AND ADMINISTRATION, DRUG ABUSE AND DEPENDENCE].

Additionally, the use of Pentazocine and Naloxone Tablets, a mixed agonist/antagonist opioid analgesic, in patients who are receiving a full opioid agonist analgesic may reduce the analgesic effect and/or precipitate withdrawal symptoms. Avoid concomitant use of Pentazocine and Naloxone Tablets with a full opioid agonist analgesic.

Risks of Driving and Operating Machinery

Pentazocine and Naloxone Tablets may impair the mental or physical abilities needed to perform potentially hazardous activities such as driving a car or operating machinery. Warn patients not to drive or operate dangerous machinery unless they are tolerant to the effects of Pentazocine and Naloxone Tablets and know how they will react to the medication.

Acute CNS Manifestations

Patients receiving therapeutic doses of Pentazocine and Naloxone Tablets have experienced hallucinations (usually visual), disorientation, and confusion which have cleared spontaneously within a period of hours. The mechanism of this reaction is not known. Such patients should be very closely observed and vital signs checked. If the drug is reinstituted, it should be done with caution since these acute CNS manifestations may recur.

The amount of naloxone present in Pentazocine and Naloxone Tablets (0.5 mg per tablet) has no action when taken orally and will not interfere with the pharmacologic action of pentazocine. However, this amount of naloxone given by injection has profound antagonistic action to narcotic analgesics.

Severe, even lethal, consequences may result from misuse of tablets by injection either alone or in combination with other substances, such as pulmonary emboli, vascular occlusion, ulceration and abscesses, and withdrawal symptoms in narcotic dependent individuals.

PRECAUTIONS

Porphyria

Particular caution should be exercised in administering pentazocine to patients with porphyria since it may provoke an acute attack in susceptible individuals.

Cardiovascular Disease

Pentazocine can elevate blood pressure, possibly through the release of endogenous catecholamines. Particular caution should be exercised in conditions where alterations in vascular resistance and blood pressure might be particularly undesirable, such as in the acute phase of myocardial infarction.

Pentazocine and Naloxone Tablets should be used with caution in patients with myocardial infarction who have nausea or vomiting.

Impaired Renal or Hepatic Function

Decreased metabolism of pentazocine by the liver in extensive liver disease may predispose to accentuation of side effects. Although laboratory tests have not indicated that pentazocine causes or increases renal or hepatic impairment, the drug should be administered with caution to patients with such impairment.

Biliary Surgery

Narcotic drug products are generally considered to elevate biliary tract pressure for varying periods following their administration. Some evidence suggests that pentazocine may differ from other marketed narcotics in this respect (i.e., it causes little or no elevation in biliary tract pressures). The clinical significance of these findings, however, is not yet known.

Information for Patients/Caregivers

Advise the patient to read the FDA-approved patient labeling (Medication Guide).

Storage and Disposal:

Because of the risks associated with accidental ingestion, misuse, and abuse, advise patients to store Pentazocine and Naloxone Tablets securely, out of sight and reach of children, and in a location not accessible by others, including visitors to the home. Inform patients that leaving Pentazocine and Naloxone Tablets unsecured can pose a deadly risk to others in the home [see WARNINGS, DRUG ABUSE AND DEPENDENCE].

Advise patients and caregivers that when medicines are no longer needed, they should be disposed of promptly. Expired, unwanted, or unused Pentazocine and Naloxone Tablets should be disposed of by flushing the unused medication down the toilet if a drug take-back option is not readily available. Inform patients that they can visit www.fda.gov/drugdisposal for a complete list of medicines recommended for disposal by flushing, as well as additional information on disposal of unused medicines.

Addiction, Abuse, and Misuse

Inform patients that the use of Pentazocine and Naloxone Tablets, even when taken as recommended, can result in addiction, abuse, and misuse, which can lead to overdose and death [see WARNINGS]. Instruct patients not to share Pentazocine and Naloxone Tablets with others and to take steps to protect Pentazocine and Naloxone Tablets from theft or misuse.

Life-Threatening Respiratory Depression

Inform patients of the risk of life-threatening respiratory depression, including information that the risk is greatest when starting Pentazocine and Naloxone Tablets or when the dosage is increased, and that it can occur even at recommended dosages.

Educate patients and caregivers on how to recognize respiratory depression and emphasize the importance of calling 911 or getting emergency medical help right away in the event of a known or suspected overdose [see WARNINGS; Life Threatening Respiratory Depression].

Accidental Ingestion

Inform patients that accidental ingestion, especially by children, may result in respiratory depression or death [see WARNINGS].

Interactions with Benzodiazepines and Other CNS Depressants

Inform patients and caregivers that potentially fatal additive effects may occur if Pentazocine and Naloxone Tablets are used with benzodiazepines or other CNS depressants, including alcohol (e.g., non-benzodiazepine, sedative/hypnotics, anxiolytics, tranquilizers, muscle relaxants, general anesthetics, antipsychotics, gabapentinoids [gabapentin or pregabalin], and other opioids), and not to use these drugs concomitantly unless supervised by a healthcare provider [see WARNINGS, PRECAUTIONS; Drug Interactions].

Patient Access to an Opioid Overdose Reversal Agent for the Emergency Treatment of Opioid Overdose

Inform patients and caregivers about opioid overdose reversal agents (e.g., naloxone, nalmefene). Discuss the importance of having access to an opioid overdose reversal agent, especially if the patient has risk factors for overdose (e.g., concomitant use of CNS depressants, a history of opioid use disorder, or prior opioid overdose) or if there are household members (including children) or other close contacts at risk for accidental ingestion or opioid overdose.

Discuss with the patient the options for obtaining an opioid overdose reversal agent (e.g., prescription, over-the-counter, or as part of a community-based program) [see WARNINGS, DOSAGE AND ADMINISTRATION].

Educate patients and caregivers on how to recognize the signs and symptoms of an overdose.

Explain to patients and caregivers that effects of opioid overdose reversal agents like naloxone and nalmefene are temporary, and that they must call 911 or get emergency medical help right away in all cases of known or suspected opioid overdose, even if an opioid overdose reversal agent is administered [see OVERDOSAGE].

Advise patients and caregivers:

- how to treat with the overdose reversal agent in the event of an opioid overdose.
- to tell family and friends about the opioid overdose reversal agent, and to keep it in a place where family and friends can access it in an emergency.
- to read the Patient Information (or other educational material) that will come with their opioid overdose reversal agent. Emphasize the importance of doing this before an opioid emergency happens, so the patient and caregiver will know what to do.

Hyperalgesia and Allodynia

Inform patients and caregivers not to increase opioid dosage without first consulting a clinician. Advise patients to seek medical attention if they experience symptoms of hyperalgesia, including worsening pain, increased sensitivity to pain, or new pain [see Warnings; Adverse Reactions].

Serotonin Syndrome

Inform patients that opioids could cause a rare but potentially life-threatening condition resulting from concomitant administration of serotonergic drugs. Warn patients of the symptoms of serotonin syndrome and to seek medical attention right away if symptoms develop. Instruct patients to inform their healthcare provider if they are taking, or plan to take serotonergic medications [see PRECAUTIONS; Drug Interactions].

Important Administration Instructions

Instruct patients how to properly take Pentazocine and Naloxone Tablets.

- Advise patients not to adjust the dose of Pentazocine and Naloxone Tablets without consulting with a physician or other healthcare professional.
- If patients have been receiving treatment with Pentazocine and Naloxone Tablets for more than a few weeks and cessation of therapy is indicated, counsel them on the importance of safely tapering the dose as abruptly discontinuation of the medication could precipitate withdrawal symptoms. Provide a dose schedule to accomplish a gradual discontinuation of the medication. [see DOSAGE AND ADMINISTRATION]

Important Discontinuation Instructions

In order to avoid developing withdrawal symptoms, instruct patients not to discontinue Pentazocine and Naloxone Tablets without first discussing a tapering plan with the prescriber [see DOSAGE AND ADMINISTRATION].

Driving or Operating Heavy Machinery

Inform patients that Pentazocine and Naloxone Tablets may impair the ability to perform potentially hazardous activities such as driving a car or operating heavy machinery. Advise patients not to perform such tasks until they know how they will react to the medication [see PRECAUTIONS].

Constipation

Advise patients of the potential for severe constipation, including management instructions and when to seek medical attention [see ADVERSE REACTIONS, CLINICAL PHARMACOLOGY].

Adrenal Insufficiency

Inform patients that opioids could cause adrenal insufficiency, a potentially life threatening condition. Adrenal insufficiency may present with non-specific symptoms and signs such as nausea, vomiting, anorexia, fatigue, weakness, dizziness, and low blood pressure. Advise patients to seek medical attention if they experience a constellation of these symptoms [see WARNINGS].

Hypotension

Inform patients that Pentazocine and Naloxone Tablets may cause orthostatic hypotension and syncope. Instruct patients how to recognize symptoms of low blood pressure and how to reduce the risk of serious consequences should hypotension occur (e.g., sit or lie down, carefully rise from a sitting or lying position) [see WARNINGS].

Anaphylaxis

Inform patients that anaphylaxis have been reported with ingredients contained in Pentazocine and Naloxone Tablets. Advise patients how to recognize such a reaction and when to seek medical attention [see CONTRAINDICATIONS, ADVERSE REACTIONS].

Pregnancy

Neonatal Opioid Withdrawal Syndrome

Inform female patients of reproductive potential that use of Pentazocine and Naloxone Tablets for an extended period of time during pregnancy can result in neonatal opioid withdrawal syndrome, which may be life-threatening if not recognized and treated [see WARNINGS, PRECAUTIONS; Pregnancy].

Embryo-Fetal Toxicity

Inform female patients of reproductive potential that Pentazocine and Naloxone Tablets can cause fetal harm and to inform the healthcare provider of a known or suspected pregnancy [see PRECAUTIONS; Pregnancy].

Lactation

Advise nursing mothers to carefully observe infants for increased sleepiness (more than usual), breathing difficulties, or limpness. Instruct nursing mothers to seek immediate medical care if they notice these signs [see PRECAUTIONS; Nursing Mothers].

Drug Interactions

Benzodiazepines and Other Central Nervous System (CNS) Depressants

Due to additive pharmacologic effect, the concomitant use of benzodiazepines or other CNS depressants including alcohol, benzodiazepines and other sedative hypnotics, anxiolytics, and tranquilizers, muscle relaxants, general anesthetics, antipsychotics, and other opioids, can increase the risk of hypotension, respiratory depression, profound sedation, coma, and death.

Reserve concomitant prescribing of these drugs for use in patients for whom alternative treatment options are inadequate. Limit dosages and durations to the minimum required. Inform patients and caregivers of this potential interaction, educate them on the signs and symptoms of respiratory depression (including sedation). If concomitant use is warranted, consider recommending or prescribing an opioid overdose reversal agent [see WARNINGS, DOSAGE and ADMINISTRATION].

Benzodiazepines and other sedatives/hypnotics, anxiolytics, tranquilizers, muscle relaxants, general anesthetics, antipsychotics, gabapentinoids [gabapentin or pregabalin], other opioids, alcohol.

Serotonergic Drugs

The concomitant use of opioids with other drugs that affect the serotonergic neurotransmitter system, such as selective serotonin reuptake inhibitors (SSRIs), serotonin and norepinephrine reuptake inhibitors (SNRIs), tricyclic antidepressants (TCAs), triptans, 5-HT3 receptor antagonists, drugs that affect the serotonin neurotransmitter system (e.g., mirtazapine, trazodone, tramadol), certain muscle relaxants (i.e., cyclobenzaprine, metaxalone), and monoamine oxidase (MAO) inhibitors (those intended to treat psychiatric disorders and also others, such as linezolid and intravenous methylene blue), has resulted in serotonin syndrome. [see PRECAUTIONS; Information for Patients].

If concomitant use is warranted, frequently evaluate the patient, particularly during treatment initiation and dose adjustment. Discontinue Pentazocine and Naloxone Tablets if serotonin syndrome is suspected.

Monoamine Oxidase Inhibitors (MAOIs)

Concomitant use of monoamine oxidase inhibitors (MAOIs) with Pentazocine and Naloxone Tablets may cause CNS excitation and hypertension through their respective effects on catecholamines. Caution should therefore be observed in administering Pentazocine and Naloxone Tablets to patients who are currently receiving MAOIs or who have received them within the preceding 14 days

Mixed Agonist/Antagonist and Partial Agonist Opioid Analgesics such as butorphanol, nalbuphine, pentazocine, buprenorphine, may reduce the analgesic effect of Pentazocine and Naloxone Tablets and/or precipitate withdrawal symptoms. Avoid concomitant use of these drugs.

Muscle Relaxants

The Concomitant use of opioids and muscle relaxants may enhance the neuromuscular blocking action of skeletal muscle relaxants and produce an increased degree of respiratory depression.

Because respiratory depression may be greater than otherwise expected, decrease the dosage of Pentazocine and Naloxone Tablets and/or the muscle relaxant (e.g., cyclobenzaprine, metaxalone) as necessary. Due to the risk of respiratory depression with concomitant use of skeletal muscle relaxants and opioids, consider recommending or prescribing an opioid overdose reversal agent [see WARNINGS, DOSAGE and ADMINISTRATION].

Diuretics

Opioids can reduce the efficacy of diuretics by inducing the release of antidiuretic hormone.

Evaluate patients for signs of diminished diuresis and/or effects on blood pressure and increase the dosage of the diuretic as needed.

Anticholinergic Drugs

The concomitant use of anticholinergic drugs may increase risk of urinary retention and/or severe constipation, which may lead to paralytic ileus.

Evaluate patients for signs of urinary retention or reduced gastric motility when Pentazocine and Naloxone Tablets is used concomitantly with anticholinergic drugs.

Tobacco

Smoking tobacco could enhance the metabolic clearance rate of pentazocine reducing the clinical effectiveness of a standard dose of pentazocine.

Carcinogenesis, Mutagenesis, Impairment of Fertility

Carcinogenesis

Long-term animal studies have not been completed to evaluate the carcinogenic potential of the combination or individual components of Pentazocine and Naloxone Tablets.

Mutagenesis

Studies to evaluate the mutagenic potential of the components of Pentazocine and Naloxone Tablets have not been conducted.

Impairment of Fertility

Studies in animals to evaluate the impact of Pentazocine and Naloxone Tablets on fertility have not been completed.

The daily administration of 4 mg/kg to 20 mg/kg pentazocine subcutaneously to female rats during a 14 day pre-mating period and until the 13th day of pregnancy did not have any adverse effects on the fertility rate.

Infertility

Use of opioids for an extended period of time may cause reduced fertility in females and males of reproductive potential. It is not known whether these effects on fertility are reversible [see ADVERSE REACTIONS].

Pregnancy

Risk Summary

Use of opioid analgesics for an extended period of time during pregnancy can cause neonatal opioid withdrawal syndrome [see WARNINGS]. There are no available data with Pentazocine and Naloxone Tablets in pregnant women to inform a drug-associated risk for major birth defects and miscarriage. In animal reproduction studies, pentazocine administered subcutaneously to pregnant hamsters during the early gestational period produced neural tube defects (i.e., exencephaly and cranioschisis) at 2.6 times the maximum daily dose (MDD). In pregnant rats administered pentazocine:naloxone during organogenesis, there were increased incidences of resorptions and extra ribs at 0.2 times the MDD. There was no evidence of malformations in rats or rabbits [see Data]. Based on animal data, advise pregnant women of the potential risk to a fetus. The estimated background risk of major birth defects and miscarriage for the indicated population is unknown. All pregnancies have a background risk of birth defect, loss, or other adverse outcomes. In the U.S. general population, the estimated background risk of major birth defects and miscarriage in clinically recognized pregnancies is 2 to 4% and 15 to 20%, respectively.

Clinical Considerations

Fetal/Neonatal Adverse Reactions

Use of opioid analgesics for an extended period of time during pregnancy for medical or nonmedical purposes can result in physical dependence in the neonate and neonatal opioid withdrawal syndrome shortly after birth.

Neonatal opioid withdrawal syndrome presents as irritability, hyperactivity and abnormal sleep pattern, high pitched cry, tremor, vomiting, diarrhea and failure to gain weight. The onset, duration, and severity of neonatal opioid withdrawal syndrome vary based on the specific opioid used, duration of use, timing and amount of last maternal use, and rate of elimination of the drug by the newborn. Observe newborns for symptoms of neonatal opioid withdrawal syndrome and manage accordingly [see WARNINGS].

Labor or Delivery

Opioids cross the placenta and may produce respiratory depression and psycho-physiologic effects in neonates. An opioid overdose reversal agent, such as naloxone or nalmefene, must be available for reversal of opioid-induced respiratory depression in the neonate. Pentazocine and Naloxone Tablets are not recommended for use in pregnant women during or immediately prior to labor, when other analgesic techniques are more appropriate. Opioid analgesics, including Pentazocine and Naloxone Tablets, can prolong labor through actions which temporarily reduce the strength, duration, and frequency of uterine contractions. However, this effect is not consistent and may be offset by an increased rate of cervical dilation, which tends to shorten labor. Monitor neonates exposed to opioid analgesics during labor for signs of excess sedation and respiratory depression.

Data

Animal Data

In a published report, a single dose of pentazocine administered to pregnant hamsters on Gestation Day 8 increased the incidence of neural tube defects (exencephaly and cranioschisis) at a dose of 196 mg/kg, SC (2.6-times the maximum daily human dose (MDD) of 600 mg/day pentazocine (12 tablets) on a mg/m^2 basis). No evidence of neural tube defects were reported following a dose of 98 mg/kg (1.3 times the MDD).

Animal reproduction studies testing the combination of pentazocine and naloxone during organogenesis have been completed in rats and rabbits. In rats, a pentazocine:naloxone dose of 64 mg/kg:0.64 mg/kg via oral gavage from Gestation Day 6 to 15 increased the incidences of resorptions and extra ribs (0.2 times the maximum daily human dose of pentazocine via 12 tablets on a mg/m^2 basis). There were no clear treatment related effects in rabbits treated from Gestation Day 6 to 18 with a pentazocine:naloxone dose of up to 64 mg/kg:0.64 mg/kg via oral gavage (0.3-times the maximum daily human dose of pentazocine via 12 tablets on a mg/m^2 basis).

Lactation

Risk Summary

Pentazocine is excreted in human milk. Caution should be exercised when Pentazocine and Naloxone Tablets are administered to a nursing woman.

The developmental and health benefits of breastfeeding should be considered along with the mother’s clinical need for Pentazocine and Naloxone Tablets and any potential adverse effects on the breastfed infant from Pentazocine and Naloxone Tablets or from the underlying maternal condition.

Clinical Considerations

Infants exposed to pentazocine and naloxone through breast milk should be monitored for excess sedation and respiratory depression. Withdrawal symptoms can occur in breastfed infants when maternal administration of an opioid analgesic is stopped, or when breast-feeding is stopped.

Pediatric Use

Safety and effectiveness in pediatric patients below the age of 12 years have not been established.

Geriatric Use

Elderly patients (aged 65 years or older) may have increased sensitivity to Pentazocine and Naloxone Tablets. In general, use caution when selecting a dosage for an elderly patient, usually starting at the low end of the dosing range, reflecting the greater frequency of decreased hepatic, renal, or cardiac function and of concomitant disease or other drug therapy.

Respiratory depression is the chief risk for elderly patients treated with opioids, and has occurred after large initial doses were administered to patients who were not opioid-tolerant or when opioids were co-administered with other agents that depress respiration. Titrate the dosage of Pentazocine and Naloxone Tablets slowly in geriatric patients and frequently reevaluate the patient [see WARNINGS].

Pentazocine and naltrexone are known to be substantially excreted by the kidney, and the risk of adverse reactions to this drug may be greater in patients with impaired renal function. Because elderly patients are more likely to have decreased renal function, care should be taken in dose selection, and it may be useful to regularly evaluate renal function.

ADVERSE REACTIONS

The following adverse reactions associated with the use of pentazocine and naltrexone were identified in clinical studies or postmarketing reports. Because some of these reactions were reported voluntarily from a population of uncertain size, it is not always possible to reliably estimate their frequency or establish a causal relationship to drug exposure.

Cardiovascular - Hypertension, hypotension, circulatory depression, tachycardia, syncope.

Respiratory - Rarely, respiratory depression.

Acute CNS Manifestations - Hallucinations (usually visual), disorientation, and confusion.

Other CNS Effects - Grand mal convulsions, increase in intracranial pressure, dizziness, lightheadedness, hallucinations, sedation, euphoria, headache, confusion, disorientation; infrequently weakness, disturbed dreams, insomnia, syncope, and depression; and rarely tremor, irritability, excitement, tinnitus.

Autonomic - Sweating; infrequently flushing; and rarely chills.

Gastrointestinal - Nausea, vomiting, constipation, diarrhea, anorexia, dry mouth, biliary tract spasm, and rarely abdominal distress.

Allergic - Edema of the face; anaphylactic shock; dermatitis, including pruritus; flushed skin, including plethora; infrequently rash, and rarely urticaria.

Ophthalmic - Visual blurring and focusing difficulty, miosis.

Hematologic - Depression of white blood cells (especially granulocytes), with rare cases of agranulocytosis, which is usually reversible, moderate transient eosinophilia.

Dependence and Withdrawal Symptoms - (See WARNINGS, PRECAUTIONS, and DRUG ABUSE AND DEPENDENCE Sections).

Other - Urinary retention, paresthesia, serious skin reactions, including erythema multiforme, Stevens-Johnson syndrome toxic epidermal necrolysis, and alterations in rate or strength of uterine contractions during labor.

- Serotonin syndrome: Cases of serotonin syndrome, a potentially life-threatening condition, have been reported during concomitant use of opioids with serotonergic drugs.
- Adrenal insufficiency: Cases of adrenal insufficiency have been reported with opioid use, more often following greater than one month of use.
- Anaphylaxis: Anaphylaxis has been reported with ingredients contained in Pentazocine and Naloxone Tablets.
- Androgen deficiency: Cases of androgen deficiency have occurred with use of opioids for an extended period of time [see Clinical Pharmacology].
- Hyperalgesia and Allodynia: Cases of hyperalgesia and allodynia have been reported with opioid therapy of any duration [see Warnings].
- Hypoglycemia: Cases of hypoglycemia have been reported in patients taking opioids. Most reports were in patients with at least one predisposing risk factor (e.g., diabetes).

Opioid-induced esophageal dysfunction (OIED): Cases of OIED have been reported in patients taking opioids and may occur more frequently in patients taking higher doses of opioids, and/or in patients taking opioids longer term [see WARNINGS].

Adverse Reactions from Observational Studies

A prospective, observational cohort study estimated the risks of addiction, abuse, and misuse in patients initiating long-term use of Schedule II opioid analgesics between 2017 and 2021. Study participants included in one or more analyses had been enrolled in selected insurance plans or health systems for at least one year, were free of at least one outcome at baseline, completed a minimum number of follow-up assessments, and either: 1) filled multiple extended-release/long-acting opioid analgesic prescriptions during a 90 day period (n=978); or 2) filled any Schedule II opioid analgesic prescriptions covering at least 70 of 90 days (n=1,244). Those included also had no dispensing of the qualifying opioids in the previous 6 months.

Over 12 months:

- approximately 1% to 6% of participants across the two cohorts newly met criteria for addiction, as assessed with two validated interview based measures of moderate-to-severe opioid use disorder based on Diagnostic and Statistical Manual of Mental Disorders, Fifth Edition (DSM-5) criteria, and
- approximately 9% and 22% of participants across the two cohorts newly met criteria for prescription opioid abuse and misuse [defined in DRUG ABUSE AND DEPENDENCE], respectively, as measured with a validated self-reported instrument.

A retrospective, observational cohort study estimated the risk of opioid involved overdose or opioid overdose-related death in patients with new long-term use of Schedule II opioid analgesics from 2006 through 2016 (n=220,249). Included patients had been enrolled in either one of two commercial insurance programs, one managed care program, or one Medicaid program for at least 9 months. New long-term use was defined as having Schedule II opioid analgesic prescriptions covering at least 70 days’ supply over the 3 months prior to study entry and none during the preceding 6 months. Patients were excluded if they had an opioid-involved overdose in the 9 months prior to study entry. Overdose was measured using a validated medical code-based algorithm with linkage to the National Death Index database. The 5-year cumulative incidence estimates for opioid-involved overdose or opioid overdose-related death ranged from approximately 1.5% to 4% across study sites, counting only the first event during follow-up. Approximately 17% of first opioid overdoses observed over the entire study period (5-11 years, depending on the study site) were fatal. Higher baseline opioid dose was the strongest and most consistent predictor of opioid-involved overdose or opioid overdose-related death. Study exclusion criteria may have selected patients at lower risk of overdose, and substantial loss to follow-up (approximately 80%) also may have biased estimates.

The risk estimates from the studies described above may not be generalizable to all patients receiving opioid analgesics, such as those with exposures shorter or longer than the duration evaluated in the studies.

DRUG ABUSE AND DEPENDENCE

Controlled Substance

Pentazocine and Naloxone Tablets contain pentazocine, a Schedule IV controlled substance.

Abuse

Pentazocine and Naloxone Tablets contains pentazocine, a substance with high potential for misuse and abuse, which can lead to the development of substance use disorder, including addiction [see Warnings].

Misuse is the intentional use, for therapeutic purposes, of a drug by an individual in a way other than prescribed by a healthcare provider or for whom it was not prescribed.

Abuse is the intentional, non-therapeutic use of a drug, even once, for its desirable psychological or physiological effects.

Drug addiction is a cluster of behavioral, cognitive, and physiological phenomena that may include a strong desire to take the drug, difficulties in controlling drug use (e.g., continuing drug use despite harmful consequences, giving a higher priority to drug use than other activities and obligations), and possible tolerance or physical dependence.

Misuse and abuse of Pentazocine and Naloxone Tablets increases risk of overdose, which may lead to central nervous system and respiratory depression, hypotension, seizures, and death. The risk is increased with concurrent abuse of Pentazocine and Naloxone Tablets with alcohol and other CNS depressants. Abuse of and addiction to opioids in some individuals may not be accompanied by concurrent tolerance and symptoms of physical dependence. In addition, abuse of opioids can occur in the absence of addiction.

All patients treated with opioids require careful and frequent reevaluation for signs of misuse, abuse, and addiction, because use of opioid analgesic products carries the risk of addiction even under appropriate medical use. Patients at high risk of Pentazocine and Naloxone Tablets abuse include those with a history of prolonged use of any opioid, including products containing pentazocine, those with a history of drug or alcohol abuse, or those who use Pentazocine and Naloxone Tablets in combination with other abused drugs.

“Drug-seeking” behavior is very common in persons with substance use disorders. Drug-seeking tactics include emergency calls or visits near the end of office hours, refusal to undergo appropriate examination, testing, or referral, repeated “loss” of prescriptions, tampering with prescriptions, and reluctance to provide prior medical records or contact information for other treating health care provider(s). “Doctor shopping” (visiting multiple prescribers to obtain additional prescriptions) is common among people who abuse drugs and people with substance use disorder. Preoccupation with achieving adequate pain relief can be appropriate behavior in a patient with inadequate pain control.

Pentazocine and Naloxone Tablets, like other opioids, can be diverted for nonmedical use into illicit channels of distribution. Careful record-keeping of prescribing information, including quantity, frequency, and renewal requests, as required by state and federal law, is strongly advised.

Proper assessment of the patient, proper prescribing practices, periodic reevaluation of therapy, and proper dispensing and storage are appropriate measures that help to limit abuse of opioid drugs.

Risks Specific to Abuse of Pentazocine and Naloxone Tablets

Abuse of Pentazocine and Naloxone Tablets poses a risk of overdose and death. The risk is increased with concurrent use of Pentazocine and Naloxone Tablets with alcohol and/or other CNS depressants.

Parenteral drug abuse is commonly associated with transmission of infectious diseases such as hepatitis and HIV.

Dependence

Both tolerance and physical dependence can develop during use of opioid therapy.

Tolerance is a physiological state characterized by a reduced response to a drug after repeated administration (i.e., a higher dose of a drug is required to produce the same effect that was once obtained at a lower dose).

Physical dependence is a state that develops as a result of a physiological adaptation in response to repeated drug use, manifested by withdrawal signs and symptoms after abrupt discontinuation or a significant dose reduction of a drug.

Withdrawal may be precipitated through the administration of drugs with opioid antagonist activity (e.g., naloxone, nalmefene), mixed agonist/antagonist analgesics (e.g., pentazocine, butorphanol, nalbuphine), or partial agonists (e.g., buprenorphine). Physical dependence may not occur to a clinically significant degree until after several days to weeks of continued use.

Do not rapidly reduce or abruptly discontinue Pentazocine and Naloxone Tablets in a patient physically dependent on opioids. Rapid tapering of Pentazocine and Naloxone Tablets in a patient physically dependent on opioids may lead to serious withdrawal symptoms, uncontrolled pain, and suicide. Rapid discontinuation has also been associated with attempts to find other sources of opioid analgesics, which may be confused with drug-seeking for abuse.

When discontinuing Pentazocine and Naloxone Tablets, gradually taper the dosage using a patient-specific plan that considers the following: the dose of Pentazocine and Naloxone Tablets the patient has been taking, the duration of treatment, and the physical and psychological attributes of the patient. To improve the likelihood of a successful taper and minimize withdrawal symptoms, it is important that the opioid tapering schedule is agreed upon by the patient. In patients taking opioids for an extended period of time at high doses, ensure that a multimodal approach to pain management, including mental health support (if needed), is in place prior to initiating an opioid analgesic taper [see DOSAGE AND ADMINISTRATION, WARNINGS].

Infants born to mothers physically dependent on opioids will also be physically dependent and may exhibit respiratory difficulties and withdrawal signs [see Pregnancy].

OVERDOSAGE

Clinical Presentation

Acute overdose with Pentazocine and Naloxone Tablets can be manifested by respiratory depression, somnolence progressing to stupor or coma, skeletal muscle flaccidity, cold and clammy skin, constricted pupils, and, in some cases, pulmonary edema, bradycardia, hypotension, hypoglycemia, partial or complete airway obstruction, atypical snoring, and death. Marked mydriasis rather than miosis may be seen with hypoxia in overdose situations. Toxic leukoencephalopathy has been reported after opioid overdose and can present hours, days, or weeks after apparent recovery from the initial intoxication.

For pentazocine alone in single doses above 60 mg there have been reports of the occurrence of nalorphine-like psychotomimetic effects such as anxiety, nightmares, strange thoughts, and hallucinations. Somnolence, marked respiratory depression associated with hypertension and tachycardia have also resulted as have seizures, hypotension, dizziness, nausea, vomiting, lethargy, and paresthesias. The respiratory depression is antagonized by naloxone (see Treatment). Circulatory failure and deepening coma may occur in more severe cases, particularly in patients who have also ingested other CNS depressants such as alcohol, sedative/hypnotics, or antihistamines.”

Treatment of Overdose

In case of overdose, priorities are the reestablishment of a patent and protected airway and institution of assisted or controlled ventilation, if needed. Employ other supportive measures (including oxygen and vasopressors) in the management of circulatory shock and pulmonary edema as indicated. Cardiac arrest or arrhythmias will require advanced life-support measures.

For clinically significant respiratory or circulatory depression secondary to pentazocine overdose, administer an opioid overdose reversal agent such as naloxone or nalmefene. As pentazocine is a mixed opioid agonist/antagonist, larger doses of naloxone or nalmefene may be needed to reverse the effects of an overdose.

In an individual physically dependent on opioids, administration of the recommended usual dosage of the overdose reversal agent will precipitate an acute withdrawal syndrome. The severity of the withdrawal symptoms experienced will depend on the degree of physical dependence and the dose of the reversal agent administered. If a decision is made to treat serious respiratory depression in the physically dependent patient, administration of the reversal agent should be begun with care and by titration with smaller than usual doses of the reversal agent.

DOSAGE AND ADMINISTRATION

Important Dosage and Administration Instructions

Pentazocine and Naloxone Tablets should be prescribed only by healthcare professionals who are knowledgeable about the use of opioids and how to mitigate the associated risks.

Use the lowest effective dosage for the shortest duration of time consistent with individual patient treatment goals [see Warnings and Precautions]. Because the risk of overdose increases as opioid doses increase, reserve titration to higher doses of Pentazocine and Naloxone Tablets for patients in whom lower doses are insufficiently effective and in whom the expected benefits of using a higher dose opioid clearly outweigh the substantial risks.

Many acute pain conditions (e.g., the pain that occurs with a number of surgical procedures or acute musculoskeletal injuries) require no more than a few days of an opioid analgesic. Clinical guidelines on opioid prescribing for some acute pain conditions are available.

There is variability in the opioid analgesic dose and duration needed to adequately manage pain due both to the cause of pain and to individual patient factors. Initiate the dosing regimen for each patient individually, taking into account the patient’s underlying cause and severity of pain, prior analgesic treatment and response, and risk factors for addiction, abuse, and misuse [see Warnings].

Respiratory depression can occur at any time during opioid therapy, especially when initiating and following dosage increases with Pentazocine and Naloxone Tablets. Consider this risk when selecting an initial dose and when making dose adjustments [see Warnings].

Patient Access to an Opioid Overdose Reversal Agent for the Emergency Treatment of Opioid Overdose

Inform patients and caregivers about opioid overdose reversal agents (e.g., naloxone, nalmefene). Discuss the importance of having access to an opioid overdose reversal agent, especially if the patient has risk factors for overdose (e.g., concomitant use of CNS depressants, a history of opioid use disorder, or prior opioid overdose) or if there are household members (including children) or other close contacts at risk for accidental ingestion or opioid overdose. The presence of risk factors for overdose should not prevent the management of pain in any patient [see WARNINGS; Addiction, Abuse, and Misuse; Life-Threatening Respiratory Depression; Risks from Concomitant Use with Benzodiazepines or Other CNS Depressants].

Discuss the options for obtaining an opioid overdose reversal agent (e.g., prescription, over-the-counter, or as part of a community-based program).

There are important differences among the opioid overdose reversal agents, such as route of administration, product strength, approved patient age range, and pharmacokinetics. Be familiar with these differences, as outlined in the approved labeling for those products, prior to recommending or prescribing such an agent.

Initial Dosage

Use of Pentazocine and Naloxone Tablets as the First Opioid Analgesic

Initiate treatment with Pentazocine and Naloxone Tablets in a dosing range of 1 tablet every three to four hours as needed for pain, at the lowest dose necessary to achieve adequate analgesia. Titrate the dose based upon the individual patient’s response to their initial dose of Pentazocine and Naloxone Tablets. This may be increased to 2 tablets when needed. Total daily dosage should not exceed 12 tablets.

Conversion from Other Opioids to Pentazocine and Naloxone Tablets

There is inter-patient variability in the potency of opioid drugs and opioid formulations. Therefore, a conservative approach is advised when determining the total daily dosage of Pentazocine and Naloxone Tablets. It is safer to underestimate a patient’s 24-hour Pentazocine and Naloxone Tablets dosage than to overestimate the 24-hour Pentazocine and Naloxone Tablets dosage and manage an adverse reaction due to overdose.

Titration and Maintenance of Therapy

Individually titrate Pentazocine and Naloxone Tablets to a dose that provides adequate analgesia and minimizes adverse reactions. Continually reevaluate patients receiving Pentazocine and Naloxone Tablets to assess the maintenance of pain control, signs and symptoms of opioid withdrawal, and other adverse reactions, as well as reassessing for the development of addiction, abuse, or misuse [see WARNINGS]. Frequent communication is important among the prescriber, other members of the healthcare team, the patient, and the caregiver/family during periods of changing analgesic requirements, including initial titration.

If the level of pain increases after dosage stabilization, attempt to identify the source of increased pain before increasing the Pentazocine and Naloxone Tablets dosage. If after increasing the dosage, unacceptable opioid-related adverse reactions are observed (including an increase in pain after dosage increase), consider reducing the dosage [see Warnings]. Adjust the dosage to obtain an appropriate balance between management of pain and opioid-related adverse reactions.

Safe Reduction or Discontinuation of Pentazocine and Naloxone Tablets

Do not rapidly reduce or abruptly discontinue Pentazocine and Naloxone Tablets in patients who may be physically dependent on opioids. Rapid reduction or abrupt discontinuation of opioid analgesics in patients who are physically dependent on opioids has resulted in serious withdrawal symptoms, uncontrolled pain, and suicide. Rapid reduction or abrupt discontinuation has also been associated with attempts to find other sources of opioid analgesics, which may be confused with drug-seeking for abuse. Patients may also attempt to treat their pain or withdrawal symptoms with illicit opioids, such as heroin, and other substances.

When a decision has been made to decrease the dose or discontinue therapy in an opioid-dependent patient taking Pentazocine and Naloxone Tablets, there are a variety of factors that should be considered, including the total daily dose of opioid (including Pentazocine and Naloxone Tablets) the patient has been taking, the duration of treatment, the type of pain being treated, and the physical and psychological attributes of the patient. It is important to ensure ongoing care of the patient and to agree on an appropriate tapering schedule and follow-up plan so that patient and provider goals and expectations are clear and realistic. When opioid analgesics are being discontinued due to a suspected substance use disorder, evaluate and treat the patient, or refer for evaluation and treatment of the substance use disorder. Treatment should include evidence-based approaches, such as medication assisted treatment of opioid use disorder. Complex patients with co-morbid pain and substance use disorders may benefit from referral to a specialist.

There are no standard opioid tapering schedules that are suitable for all patients. Good clinical practice dictates a patient-specific plan to taper the dose of the opioid gradually. For patients on Pentazocine and Naloxone Tablets who are physically opioid-dependent, initiate the taper by a small enough increment (e.g., no greater than 10% to 25% of the total daily dose) to avoid withdrawal symptoms, and proceed with dose-lowering at an interval of every 2 to 4 weeks. Patients who have been taking opioids for briefer periods of time may tolerate a more rapid taper.

It may be necessary to provide the patient with lower dosage strengths to accomplish a successful taper. Reassess the patient frequently to manage pain and withdrawal symptoms, should they emerge. Common withdrawal symptoms include restlessness, lacrimation, rhinorrhea, yawning, perspiration, chills, myalgia, and mydriasis. Other signs and symptoms also may develop, including irritability, anxiety, backache, joint pain, weakness, abdominal cramps, insomnia, nausea, anorexia, vomiting, diarrhea, or increased blood pressure, respiratory rate, or heart rate. If withdrawal symptoms arise, it may be necessary to pause the taper for a period of time or raise the dose of the opioid analgesic to the previous dose, and then proceed with a slower taper. In addition, evaluate patients for any changes in mood, emergence of suicidal thoughts, or use of other substances.

When managing patients taking opioid analgesics, particularly those who have been treated for an extended period of time, and/or with high doses for chronic pain, ensure that a multimodal approach to pain management, including mental health support (if needed), is in place prior to initiating an opioid analgesic taper. A multimodal approach to pain management may optimize the treatment of chronic pain, as well as assist with the successful tapering of the opioid analgesic [see WARNINGS/Withdrawal, DRUG ABUSE AND DEPENDENCE].

HOW SUPPLIED

Pentazocine and Naloxone Tablets, USP are light green, scored, capsule shaped tablets debossed 395 to the left of the score, 50 over 0.5 to the right of the score and WATSON on the reverse side supplied in bottles of 100.

Bottles of 100 ………………………………….. NDC 0591-0395-01

Store at 20° to 25°C (68° to 77°F) [See USP Controlled Room Temperature].

Dispense in a tight, light-resistant container as defined in the USP.

Store Pentazocine and Naloxone Tablets, USP securely and dispose of properly [see PRECAUTIONS/Information for Patients].

Manufactured In India By:
Watson Pharma Private Limited
Verna, Salcette Goa 403 722 INDIA

Manufactured For:
Teva Pharmaceuticals
Parsippany, NJ 07054
Rev. L 10/2025

Medication Guide
Pentazocine and Naloxone (pen tazʹ oh seen and nal oxʹ one)
Tablets, USP
CIV

Pentazocine and Naloxone Tablets are:

- A strong prescription pain medicine that contains an opioid (narcotic) that is used to manage moderate to severe pain, when other pain treatments such as non-opioid pain medicines do not treat your pain well enough or you cannot tolerate them.
- An opioid pain medicine that can put you at risk for overdose and death. Even if you take your dose correctly as prescribed you are at risk for opioid addiction, abuse, and misuse that can lead to death.

Important information about Pentazocine and Naloxone Tablets:

- Get emergency help or call 911 right away if you take too many Pentazocine and Naloxone Tablets (overdose). When you first start taking Pentazocine and Naloxone Tablets, when your dose is changed, or if you take too much (overdose), serious or life-threatening breathing problems that can lead to death may occur. Ask your healthcare provider about medicines like naloxone or nalmefene that can be used in an emergency to reverse an opioid overdose.
- Taking Pentazocine and Naloxone Tablets with other opioid medicines, benzodiazepines, gabapentinoids (gabapentin or pregabalin), alcohol, or other central nervous system depressants (including street drugs) can cause severe drowsiness, decreased awareness, breathing problems, coma, and death.
- Never give anyone else your Pentazocine and Naloxone Tablets. They could die from taking it. Selling or giving away Pentazocine and Naloxone Tablets is against the law.
- Store Pentazocine and Naloxone Tablets securely, out of sight and reach of children, and in a location not accessible by others, including visitors to the home.

Do not take Pentazocine and Naloxone Tablets if you have:

- severe asthma, trouble breathing, or other lung problems.
- a bowel blockage or have narrowing of the stomach or intestines.
- previously had an allergic reaction to pentazocine or naloxone.
- known or suspected gastrointestinal obstruction, including paralytic ileus.

Before taking Pentazocine and Naloxone Tablets, tell your healthcare provider if you have a history of:

• head injury, seizures

• liver, kidney, thyroid problems

• problems urinating

• pancreas or gallbladder problems

• abuse of street or prescription drugs, alcohol addiction, opioid overdose, or mental health problems.

Tell your healthcare provider if you are:

- noticing your pain getting worse. If your pain gets worse after you take Pentazocine and Naloxone Tablets, do not take more of Pentazocine and Naloxone Tablets without first talking to your healthcare provider. Talk to your healthcare provider if the pain that you have increases, if you feel more sensitive to pain, or if you have new pain after taking Pentazocine and Naloxone Tablets.
- pregnant or planning to become pregnant. Use of Pentazocine and Naloxone Tablets for an extended period of time during pregnancy can cause withdrawal symptoms in your newborn baby that could be life-threatening if not recognized and treated.
- breastfeeding. Pentazocine and naloxone passes into breast milk and may harm your baby. Carefully observe infants for increased sleepiness (more than usual), breathing difficulties, or limpness. Seek immediate medical care if you notice these signs.
- living in a household where there are small children or someone who has abused street or prescription drugs
- taking prescription or over-the-counter medicines, vitamins, or herbal supplements. Taking Pentazocine and Naloxone Tablets with certain other medicines can cause serious side effects that could lead to death.

When taking Pentazocine and Naloxone Tablets:

- Do not change your dose. Take Pentazocine and Naloxone Tablets exactly as prescribed by your healthcare provider. Use the lowest dose possible for the shortest time needed.
- For acute (short-term) pain, you may only need to take Pentazocine and Naloxone Tablets for a few days. You may have some Pentazocine and Naloxone Tablets left over that you did not use. See disposal information at the bottom of this section for directions on how to safely throw away (dispose of) your unused Pentazocine and Naloxone Tablets.
- Take your prescribed dose every 3 or 4 hours at the same time every day as needed for pain. Do not take more than your prescribed dose. If you miss a dose, take your next dose at your usual time.
- Call your healthcare provider if the dose you are taking does not control your pain.
- If you have been taking Pentazocine and Naloxone Tablets regularly, do not stop taking Pentazocine and Naloxone Tablets without talking to your healthcare provider.
- Dispose of expired, unwanted, or unused Pentazocine and Naloxone Tablets by promptly flushing down the toilet, if a drug take-back option is not readily available. Visit www.fda.gov/drugdisposal for additional information on disposal of unused medicines.

While taking Pentazocine and Naloxone Tablets DO NOT:

- Drive or operate heavy machinery, until you know how Pentazocine and Naloxone Tablets affect you. Pentazocine and Naloxone Tablets can make you sleepy, dizzy, or lightheaded.
- Drink alcohol or use prescription or over-the-counter medicines that contain alcohol. Using products containing alcohol during treatment with Pentazocine and Naloxone Tablets may cause you to overdose and die.

The possible side effects of Pentazocine and Naloxone Tablets:
• constipation, nausea, sleepiness, vomiting, tiredness, headache, dizziness, abdominal pain. Call your healthcare provider if you have any of these symptoms and they are severe.
Get emergency medical help or call 911 right away if you have:
• trouble breathing, shortness of breath, fast heartbeat, chest pain, swelling of your face, tongue, or throat, extreme drowsiness, light-headedness when changing positions, feeling faint, agitation, high body temperature, trouble walking, stiff muscles, or mental changes such as confusion.
These are not all the possible side effects of Pentazocine and Naloxone Tablets. Call your healthcare provider for medical advice about side effects. You may report side effects to FDA at 1-800-FDA-1088. For more information go to dailymed.nlm.nih.gov.
For more information call Teva at 1-888-838-2872.

This Medication Guide has been approved by the U.S. Food and Drug Administration.

Manufactured In India By:
Watson Pharma Private Limited
Verna, Salcette Goa 403 722 INDIA

Manufactured For:
Teva Pharmaceuticals
Parsippany, NJ 07054
Rev. G 8/2025

Principal Display Panel

NDC 0591-0395-01
CIV
Pentazocine and Naloxone Tablets, USP
50 mg*/0.5mg*
PHARMACIST: Dispense the accompanying Medication Guide to each patient.
Rx only
100 Tablets